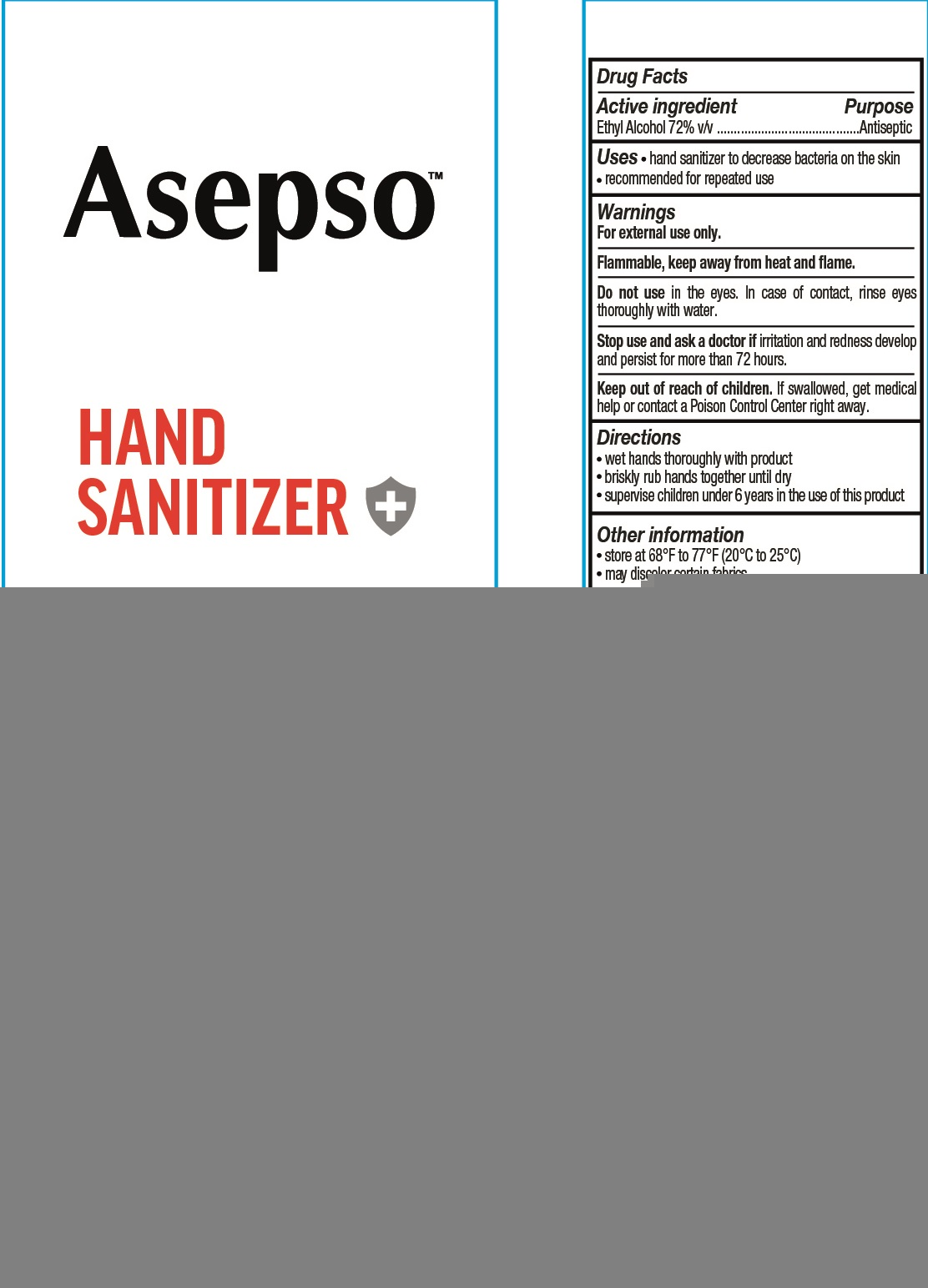 DRUG LABEL: Asepso Hand Sanitizer
NDC: 73931-014 | Form: LIQUID
Manufacturer: Guangdong Essence Daily Chemical Co., Ltd
Category: otc | Type: HUMAN OTC DRUG LABEL
Date: 20200704

ACTIVE INGREDIENTS: ALCOHOL 72 mL/100 mL
INACTIVE INGREDIENTS: WATER; GLYCERIN; TROLAMINe; ALOE VERA LEAF

Active ingredient

Ethyl Alcohol 72% v/v

Purpose

Antiseptic

Use

- A hand sanitizer to decrease bacteria on the skin.
- Recomended for repeated use.

Warnings

For external use only.

Flammable,

Keep product away from heat or flame.

When using this product

do not use in the eyes, In case of contact, rinse eyes thoroughly with water.

Stop use and ask a doctor if

irritation or redness develop and persist for more than 72 hours.

Keep out of reach of children.

If swallowed, get medical help or contact a Poison Control Center right away.

Directions

- Wet hands thoroughly with product.
- Briskly rub hands together until dry
- Supervise children under 6 years in the use of this product.

Inactive ingredients

Water, Glycerin, Carbomer, Triethanolamine, Aloe Barbadensis Leaf Juice.

Other information

- Store at68℉ to 77℉ （20℃ to 25℃).
- May discolor certain fabrics.